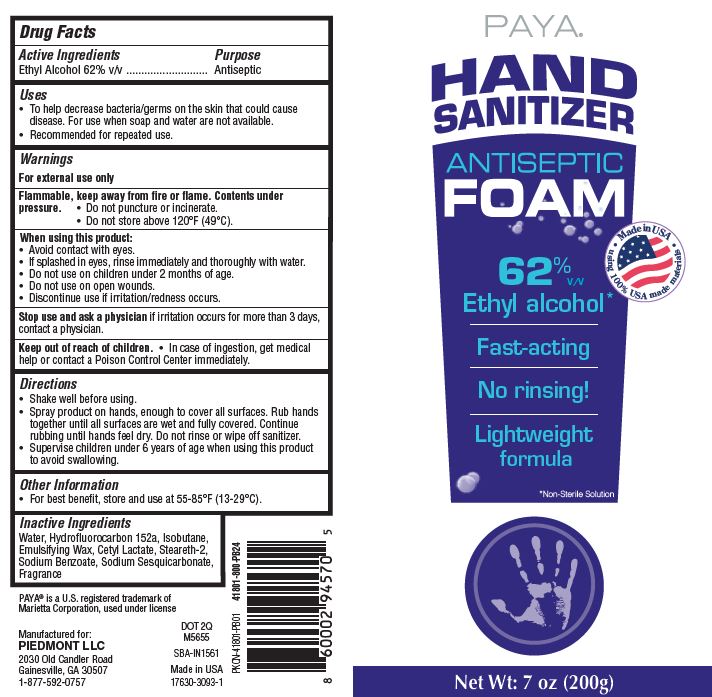 DRUG LABEL: Foaming Mousse Hand Sanitizer
NDC: 17630-3093 | Form: AEROSOL, FOAM
Manufacturer: Accra Pac, Inc. (DBA KIK-Indiana)
Category: otc | Type: HUMAN OTC DRUG LABEL
Date: 20200410

ACTIVE INGREDIENTS: ALCOHOL 62 mL/100 mL
INACTIVE INGREDIENTS: .ALPHA.-TOCOPHEROL ACETATE; TROLAMINE; GLYCERIN; WATER

Paya® Hand Sanitizer Antiseptic Foam

Active Ingredient

Ethyl Alcohol 62% v/v

Purpose

Antiseptic

Uses

- To help decrease bact:eriafgerms on the sk!in that could cause

disease. For use when soap and water are not available.

- Recommended for repeated use.

Warnings

For external use only

• Do not puncture or incinerate.

• Do not store above 120°F (49°C).

When using this product

• Avoid contact with eyes.
• It splashed in eyes, rinse immediately and thoroughly with water.
• Do not use on chil'dren under 2 months of age.
• Do not use on open wounds.
• Discontinue use if irritation/redness occurs.

Stop use and ask a physician if irritation occurs for more than 3 days, contact a physician.

Keep out of reach of children

• In case of ingestion, get medical help or contact a Poison Control Center immediately.

Directions

• Shake well before using.
• Spray product on hands, enough to cover all surfaces. Rub hands together until all surfaces are wet and fully covered. Continue rubbing untiil hands feel dry. Do not rinse or wipe off sanitizer.
• Supervise children under 6 years of age when using this product to avoid swallowing.

Dosage & Administration

• Spray product on hands, enough to cover all surfaces. Rub hands together until all surfaces are wet and fully covered. Continue rubbing untiil hands feel dry. Do not rinse or wipe off sanitizer.

Other Information

• For best benefit, store and use are 55-85° F (13-29°C).

Inactive Ingredient

Water, Hydrofluorocarbon 152a, lsobutane, Emulsifying Wax., Cetyl Lactate, Steareth-2, Sodium Benzoate, Sodium Sesquicarbonate.
Fragrance

Principal Display Panel

200 mL NDC: 17630-3093-1

Paya®

HAND

SANITIZER

ANTISEPTIC

FOAM

62% v/v

Ethyl alcohol*

Fast-acting

No Rinsing!

Lightweight

formula

*Non-Sterile Solution.

Net Wt: 7 oz (200g)